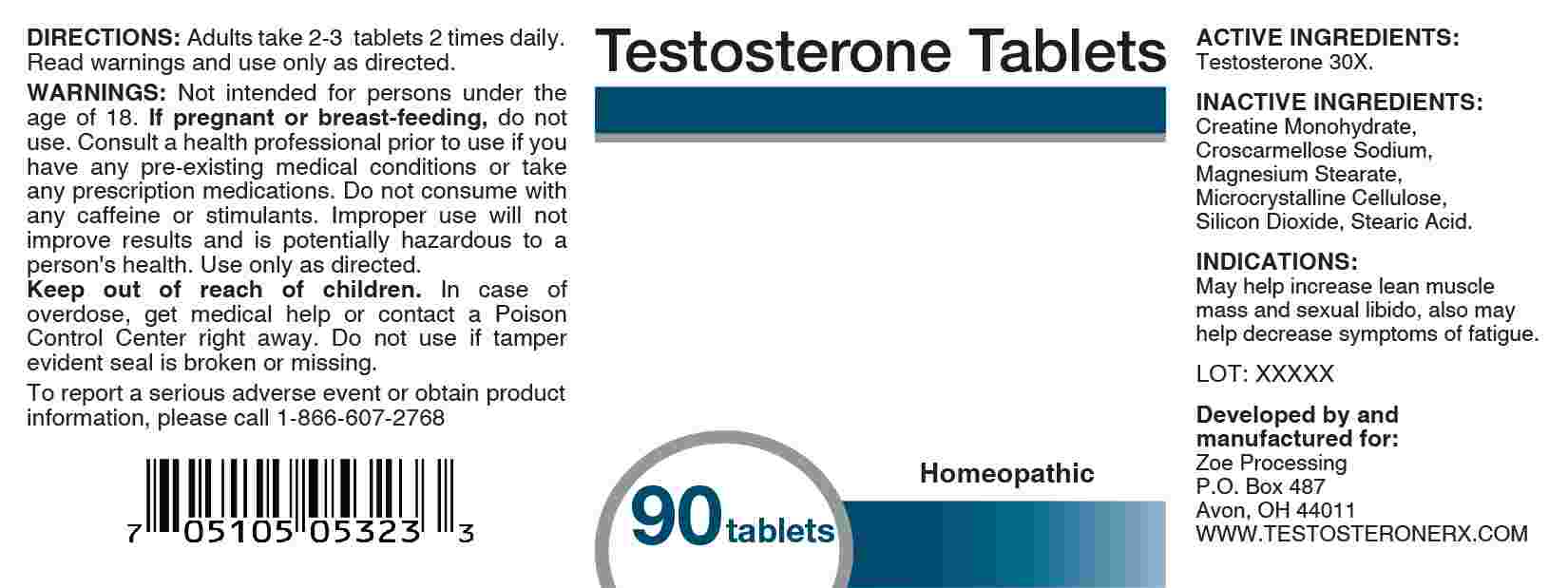 DRUG LABEL: Testosterone
NDC: 44117-0003 | Form: TABLET
Manufacturer: Zoe Processing
Category: homeopathic | Type: HUMAN OTC DRUG LABEL
Date: 20250203
DEA Schedule: CIII

ACTIVE INGREDIENTS: TESTOSTERONE 30 [hp_X]/1 1
INACTIVE INGREDIENTS: CREATINE MONOHYDRATE; CROSCARMELLOSE SODIUM; MAGNESIUM STEARATE; MICROCRYSTALLINE CELLULOSE; SILICON DIOXIDE; STEARIC ACID

DRUG FACTS:

ACTIVE INGREDIENT:

Testosterone 30X.

PURPOSE:

May help increase lean muscle mass and sexual libido, also may help decrease symptoms of fatigue.

WARNINGS:

Not intended for persons under the age of 18.

If pregnant or breast-feeding, do not use.

Consult a health professional prior to use if you have any pre-existing medical conditions or take any prescription medications.

Do not consume with any caffeine or stimulants. Improper use will not improve results and is potentially hazardous to a person's health.

Use only as directed.

Keep out of reach of children. In case of overdose, get medical help or contact a Poison Control Center right away.

Do not use if tamper evident seal is broken or missing.

KEEP OUT OF REACH OF CHILDREN:

In case of overdose, get medical help or contact a Poison Control Center right away.

DIRECTIONS:

Adults take 2-3 tablets 2 times daily. Read warnings and use only as directed.

INDICATIONS:

May help increase lean muscle mass and sexual libido, also may help decrease symptoms of fatigue.

INACTIVE INGREDIENTS:

Creatine Monohydrate, Croscarmellose Sodium, Magnesium Stearate, Microcrystalline Cellulose, Silicon Dioxide, Stearic Acid.

QUESTIONS:

Developed by and manufactured for:

Zoe Processing

P.O. Box 487

Avon, OH 44011

WWW.TESTOSTERONERX.COM

To report a serious adverse event or obtain product information, please call 1-866-607-2768.

PACKAGE LABEL DISPLAY:

Testosterone Tablets

Homeopathic

90 tablets